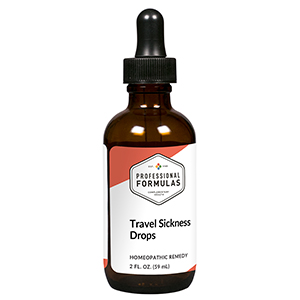 DRUG LABEL: Travel Sickness Drops
NDC: 63083-2075 | Form: LIQUID
Manufacturer: Professional Complementary Health Formulas
Category: homeopathic | Type: HUMAN OTC DRUG LABEL
Date: 20190815

ACTIVE INGREDIENTS: AETHUSA CYNAPIUM WHOLE 6 [hp_X]/59 mL; IPECAC 6 [hp_X]/59 mL; AMBERGRIS 12 [hp_X]/59 mL; APOMORPHINE HYDROCHLORIDE 12 [hp_X]/59 mL; ANAMIRTA COCCULUS FRUIT 12 [hp_X]/59 mL; COLCHICUM AUTUMNALE BULB 12 [hp_X]/59 mL; LIQUID PETROLEUM 12 [hp_X]/59 mL; STRYCHNOS NUX-VOMICA SEED 30 [hp_X]/59 mL; VERATRUM ALBUM ROOT 30 [hp_X]/59 mL
INACTIVE INGREDIENTS: ALCOHOL; WATER

C75

ACTIVE INGREDIENTS

Aethusa cynapium 6X
Ipecacuanha 6X
Ambra grisea 12X
Apomorphinum muriaticum 12X
Cocculus indicus 12X
Colchicum autumnale 12X
Petroleum 12X
Nux vomica 30X
Veratrum album 30X

QUESTIONS

Professional Formulas

PO Box 2034 Lake Oswego, OR 97035

INDICATIONS

For the temporary relief of motion sickness, fatigue, uneasiness, dizziness, nausea, or vomiting.*

PURPOSE

*Claims based on traditional homeopathic practice, not accepted medical evidence. Not FDA evaluated.

WARNINGS

In case of overdose, get medical help or contact a poison control center right away.

Keep out of the reach of children.

PREGNANCY OR BREAST FEEDING

If pregnant or breastfeeding, ask a healthcare professional before use.

DIRECTIONS

Place drops under tongue 30 minutes before/after meals. Adults and children 12 years and over: Take 10 drops up to 3 times per day for up to 6 weeks. For immediate onset of symptoms, take 10 to 15 drops every 15 minutes up to 3 hours. For less severe symptoms, take 10-15 drops hourly up to 8 hours. Consult a physician for use in children under 12 years of age.

OTHER INFORMATION

Tamper resistant. If seal is broken, do not use. After opening, close container tightly and store at room temperature away from heat.

INACTIVE INGREDIENTS

20% ethanol, purified water.

LABEL

Est 1985

Professional Formulas

Complementary Health

Travel Sickness Drops

Homeopathic Remedy

2 FL. OZ. (59 mL)